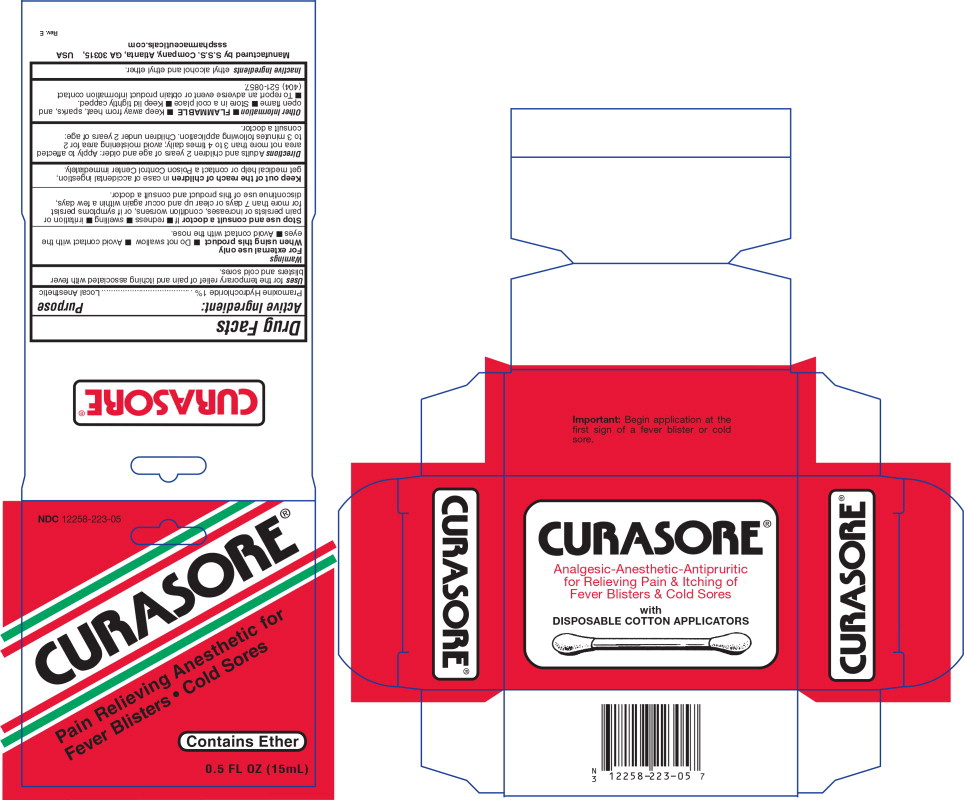 DRUG LABEL: Curasore
NDC: 12258-223 | Form: LIQUID
Manufacturer: S.S.S. Company
Category: otc | Type: HUMAN OTC DRUG LABEL
Date: 20260108

ACTIVE INGREDIENTS: PRAMOXINE HYDROCHLORIDE 1 g/100 mL
INACTIVE INGREDIENTS: ALCOHOL; ETHER

DRUG FACTS

Active Ingredient:

Pramoxine Hydrochloride 1%

Purpose:

Local Anesthetic

Uses

For the temporary relief of pain and itching associated with fever blisters and cold sores

Warnings

For external use only

When using this product

- Do not swallow
- Avoid contact with the eyes
- Avoid contact with the nose

Stop use and consult a doctor If

- Redness
- Swelling
- Irritation or pain persists or increases, condition worsens, or if symptoms persist for more than 7 days or clear up and occur again within a few days, discontinue use of this product and consult a doctor.

Keep out of the reach of children

In case of accidental ingestion, get medical help or contact a Poison Control Center immediately.

Directions

Adults and children 2 years of age and older: Apply to affected area not more than 3 to 4 times daily; avoid moistening area for 2 to 3 minutes following application. Children under 2 years of age: consult a doctor.

Other Information

- FLAMMABLE
- Keep away from heat, sparks, and open flame
- Store in a cool place
- Keep lid tightly capped.
- To report an adverse event or obtain product information contact (404) 521-0857.

Inactive Ingredients

ethyl alcohol and ethyl ether

Principal Display Panel

NDC 12258-223-05

CURASORE®

Pain Relieving Anesthetic for

Fever Blisters • Cold Sores

Contains Ether

0.5 FL OZ (15mL)

Important: Begin application at the

first sign of a fever blister or cold

sore.

CURASORE®

Analgesic-Anesthetic-Antipruritic

for Relieving Pain & Itching of

Fever Blisters & Cold Sores

With

DISPOSABLE COTTON APPLICATORS

Other Packaging Content

Manufactured by S.S.S. Company, Atlanta, GA 30315, USA

ssspharmaceuticals.com

Rev. E